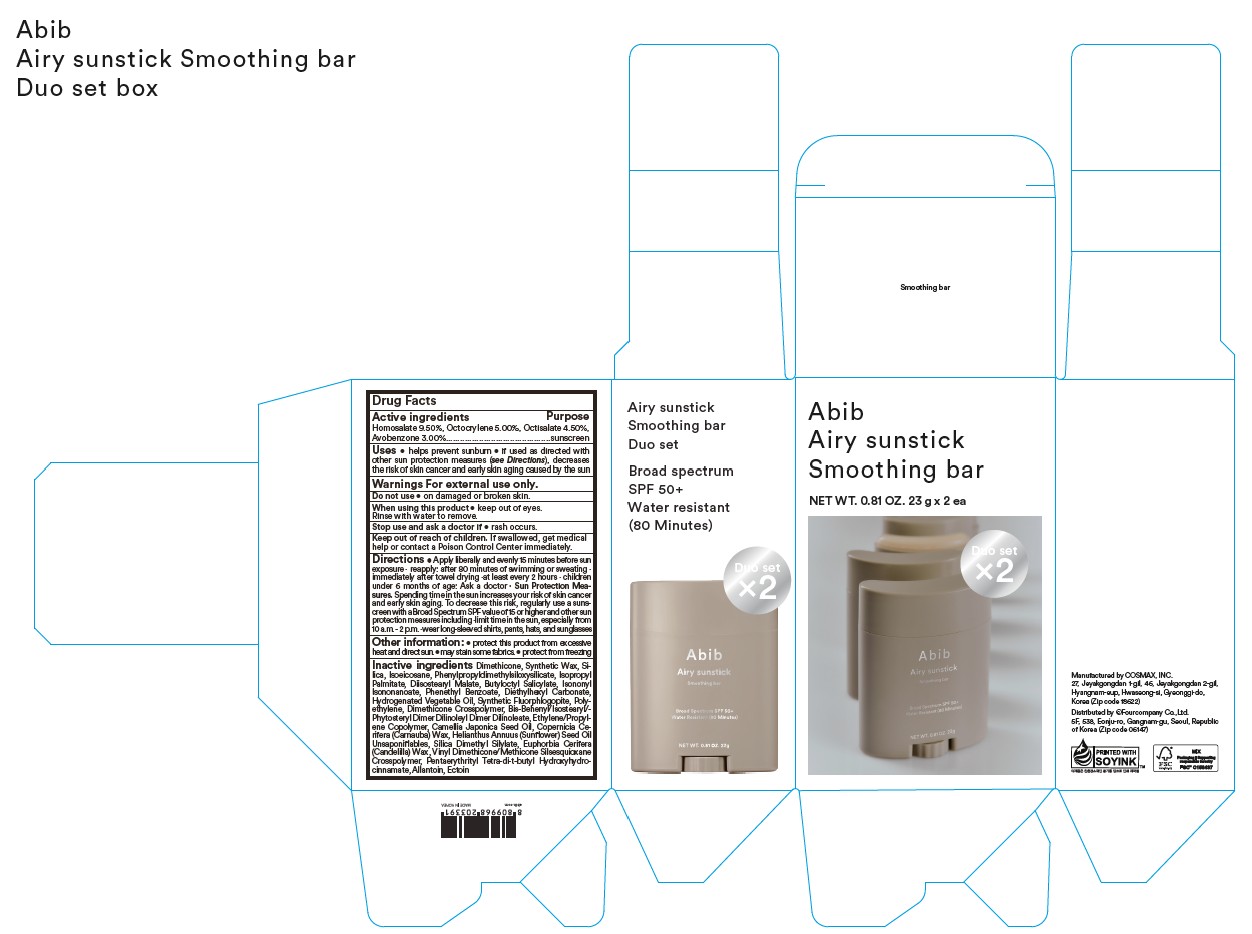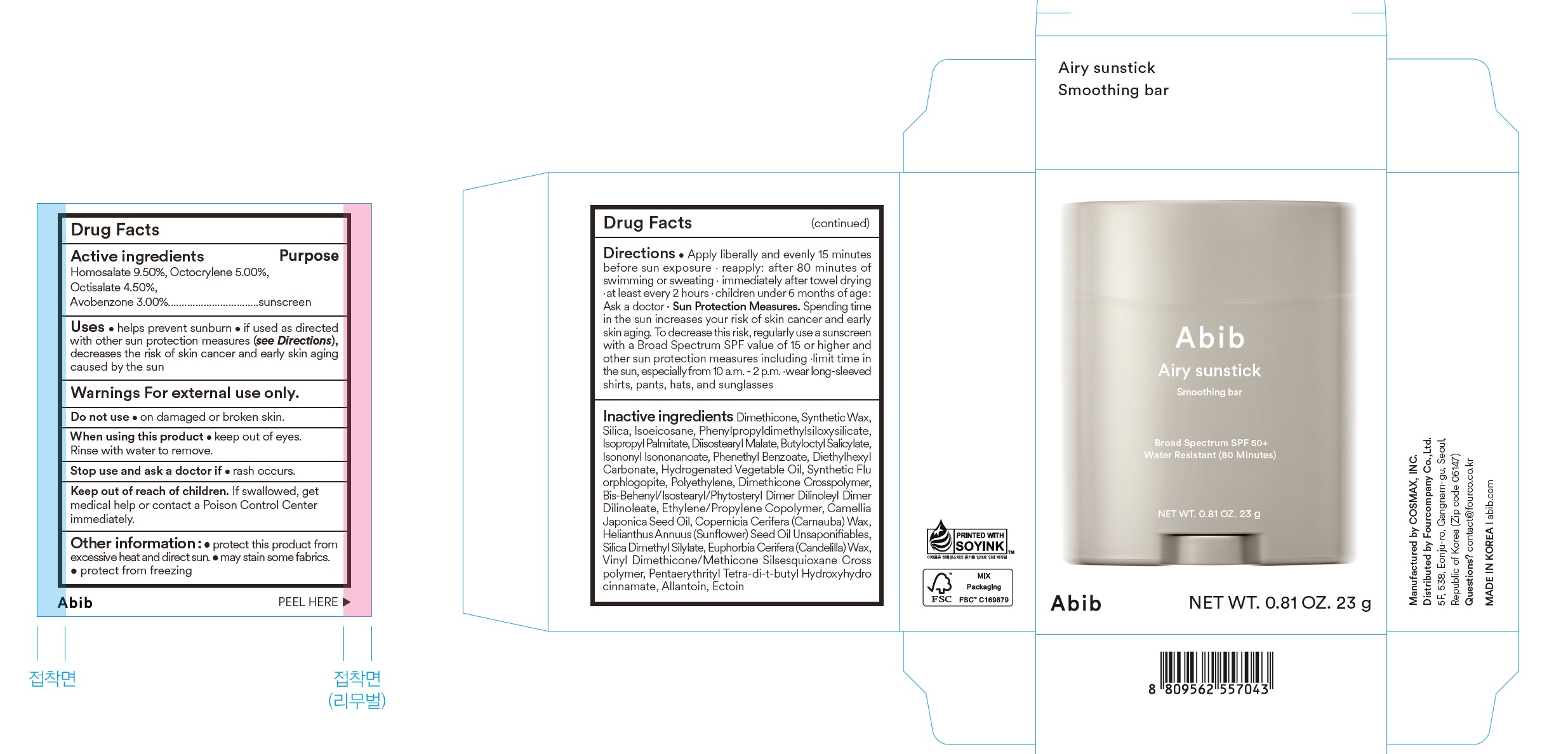 DRUG LABEL: Airy sunstick smooting bar
NDC: 73676-116 | Form: STICK
Manufacturer: FOURCOMPANY CO., LTD.
Category: otc | Type: HUMAN OTC DRUG LABEL
Date: 20251023

ACTIVE INGREDIENTS: HOMOSALATE 9.5 g/100 g; OCTOCRYLENE 5 g/100 g; OCTISALATE 4.5 g/100 g; AVOBENZONE 3 g/100 g
INACTIVE INGREDIENTS: DIETHYLHEXYL CARBONATE; ALLANTOIN; SUNFLOWER OIL UNSAPONIFIABLES; MAGNESIUM POTASSIUM ALUMINOSILICATE FLUORIDE; BUTYLOCTYL SALICYLATE; VINYL DIMETHICONE/METHICONE SILSESQUIOXANE CROSSPOLYMER; ECTOINE; SILICON DIOXIDE; SYNTHETIC WAX (1200 MW); PHYTOSTERYL/ISOSTEARYL/CETYL/STEARYL/BEHENYL DIMER DILINOLEATE; PPG-15; POLYMETHYLSILSESQUIOXANE/TRIMETHYLSILOXYSILICATE; DIMETHICONE; ISOEICOSANE; DIISOSTEARYL MALATE; ISONONYL ISONONANOATE; CAMELLIA JAPONICA SEED OIL; SILICA DIMETHYL SILYLATE; HYDROGENATED PALM KERNEL OIL; PENTAERYTHRITOL TETRAKIS(3-(3,5-DI-TERT-BUTYL-4-HYDROXYPHENYL)PROPIONATE); HIGH DENSITY POLYETHYLENE; PHENETHYL BENZOATE; ISOPROPYL PALMITATE; DIMETHICONE CROSSPOLYMER (450000 MPA.S AT 12% IN CYCLOPENTASILOXANE); CARNAUBA WAX; CANDELILLA WAX

Abib
Airy sunstick
Smoothing Bar

Active ingredients

Homosalate 9.50%, Octocrylene 5.00%, Octisalate 4.50%, Avobenzone 3.00%

Purpose sunscreen

Uses

- help prevent sunburn
- if used as directed with other sun protection measures (see Directions), deacreases the risk of skin cancer and early skin aging caused by the sun

Warnings For external use only.

Do not use on damaged or broken skin

When using this product keep out of eyes. Rinse with water to remove

Stop use and ask a doctor if rash occurs

Keep out of reach of children. If swallowed, get medical help or contact a Poison Control Center immediately.

Other information: protect this product from excessive heat and direct sun. may stain some fabrics. protect from freezing

DOSAGE AND ADMINISTRATION

Directions apply liberally and evenly 15 minutes before sun exposure. reapply: after 80 minutes of swimming or sweating. immediately after towel drying. at least every 2 hours. children under 6 months of age: ask a doctor. Sun protection measures. spending time in the sun increases your risk of skin cancer and early aging. To decrease this risk, regularly use a sunscreen with a Broad Spectrum SPF value of 15 or higher and other sun protection measures including: limit time in the sun, especially from 10 a.m. - 2 p.m., wear long-sleeved shirts, pants, hats, and sunglasses

INACTIVE INGREDIENT

Actives ingredients Dimethicone, Synthetic Wax, Silica, Isoeicosane, Phenylpropy ldimethylsiloxy silicate, Isopropyl Palmitate, Disostearyl Malate, Butylocty/ Salicylate, Isononyl Isononanoate, Phenethyl Benzoate, Diethylhexyl Carbonate, Hydrogenated Vegetable Oil, Synthetic Fluorphlogopite, Polyethylene, Dimethicone Crosspolymer, Bis-Behenyl/Isostearyl/Phytosteryl Dimer Dilinoleyl Dimer Dilinoleate, Ethylene/Propylene Copolymer, Camellia Japonica Seed Oil,Copernicia Cerifera (Carnauba) Wax, Helianthus Annuus (Sunflower) Seed Oil Unsaponifiables, Silica Dimethyl Silylate, Euphorbia Cerifera (Candelilla) Wax, Vinyl Dimethicone/Methicone Silsesquioxane Crosspolymer, Pentaerythrityl Tetra-di-t-butyl Hydroxyhydrocinnamate, Allantoin, Ectoin

Abib Airy sunstick - 0.81 oz / 23g

Abib
Airy sunstick
Smoothing bar

Broad Spectrum SPF 50+

Water Resistant (80 Minutes)

NET WT. 0.81 OZ. 23g

Abib Airy sunstick Duo Set - 0.81 oz / 23g x 2 ea

Abib

Airy sunstick

Smoothing bar

NET WT. 0.81 OZ. / 23g x 2 ea